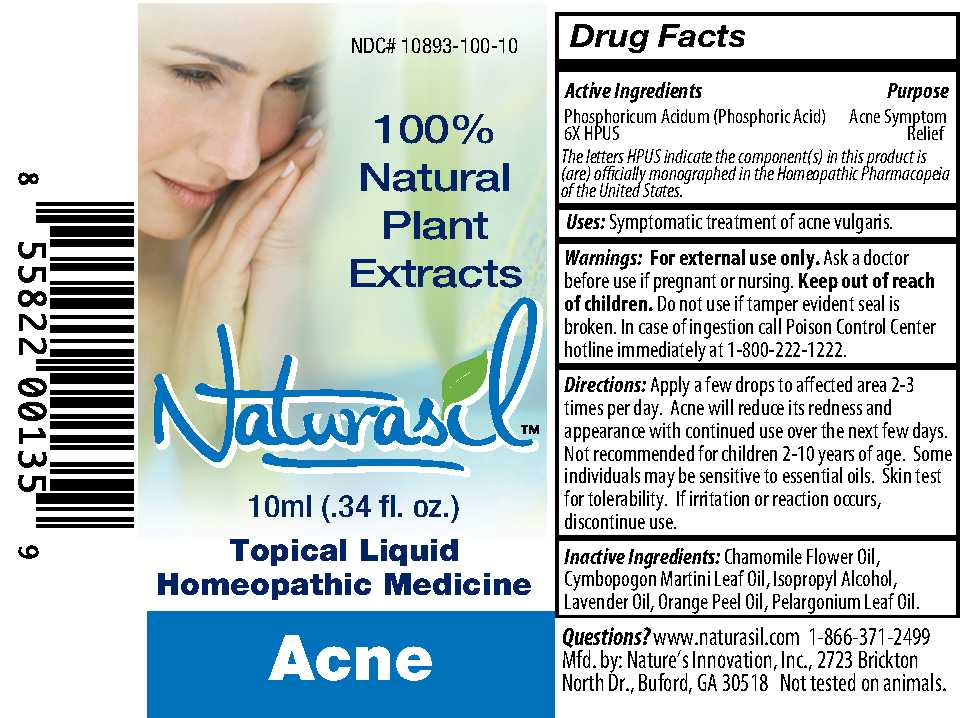 DRUG LABEL: Naturasil
NDC: 10893-100 | Form: LIQUID
Manufacturer: Nature's Innovation, Inc.
Category: homeopathic | Type: HUMAN OTC DRUG LABEL
Date: 20210114

ACTIVE INGREDIENTS: PHOSPHORIC ACID 6 [hp_X]/10 mL
INACTIVE INGREDIENTS: CHAMOMILE FLOWER OIL; PALMAROSA OIL; ISOPROPYL ALCOHOL; LAVENDER OIL; ORANGE PEEL; GERANIUM OIL, ALGERIAN TYPE

Naturasil Acne 10ml labeling

Warnings

Warnings: For external use only.

Ask a doctor before use if pregnant or nursing.

Keep out of reach of children.

Do not use if tamper evident seal is broken.

OTHER SAFETY INFORMATION

In case of ingestion call Poison Control Center hotline immediately at 1-800-222-1222.

Inactive Ingredients

Inactive Ingredients: Chamomile Flower Oil, Cymbopogon Martini Leaf Oil, Isopropyl Alcohol, Lavender Oil, Orange Peel Oil, Pelargonium Leaf Oil.

DOSAGE AND ADMINISTRATION

Directions: Apply a few drops to affected area 2-3 times per day. Acne will reduce its redness and appearance with continued use over the next few days. Not recommended for children 2-10 years of age. Some individuals may be sensitive to essential oils. Skin test for tolerability. If irritation or reaction occurs, discontinue use.

Uses

Uses: Symptomatic treatment of acne vulgaris.

Questions

Questions? www.naturasil.com 1-866-371-2449
Mfd. by: Nature's Innovation, Inc., 2723 Brickton
North Dr., Buford, GA 30518 Not tested on animals.

Active Ingredients

Phosphoricum Acidum (Phosphoric Acid)

6X HPUS

Purpose

Acne Symptom Relief

PACKAGE LABEL

100% Natural Plant Extracts
Naturasil
10 ml (.34 fl. oz.)
Topical Liquid Homeopathic Medicine
Acne